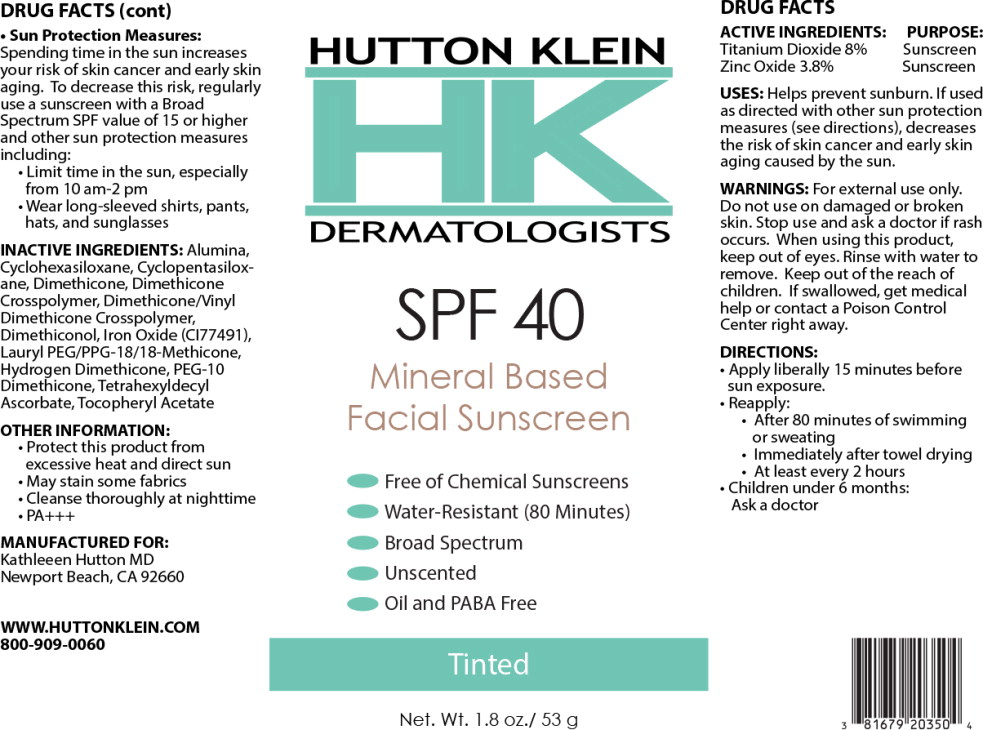 DRUG LABEL: HUTTON KLEIN HK DERMATOLOGISTS SPF 40 Mineral Based Facial Sunscreen Tinted
NDC: 81679-203 | Form: CREAM
Manufacturer: Hutton, Kathleen MD
Category: otc | Type: HUMAN OTC DRUG LABEL
Date: 20250116

ACTIVE INGREDIENTS: Titanium Dioxide 80 mg/1 g; Zinc Oxide 38 mg/1 g
INACTIVE INGREDIENTS: Aluminum Hydroxide; Cyclomethicone 6; Cyclomethicone 5; Dimethicone 20; Dimethicone Crosspolymer (450000 MPA.S AT 12% in Cyclopentasiloxane); Dimethicone/Vinyl Dimethicone Crosspolymer (Soft Particle); Dimethiconol (2000 CST); Brown Iron Oxide; Lauryl PEG/PPG-18/18 Methicone; Hydrogen Dimethicone (20 CST); PEG-10 Dimethicone (600 CST); Tetrahexyldecyl Ascorbate; .Alpha.-Tocopherol Acetate

DRUG FACTS

ACTIVE INGREDIENTS:

Titanium Dioxide 8%

Zinc Oxide 3.8%

PURPOSE:

Sunscreen

Sunscreen

USES:

Helps prevent sunburn. If used as directed with other sun protection measures (see directions), decreases the risk of skin cancer and early skin aging caused by the sun.

WARNINGS:

For external use only.

Do not use on damaged or broken skin.

Stop use and ask a doctor if rash occurs.

When using this product, keep out of eyes. Rinse with water to remove.

KEEP OUT OF REACH OF CHILDREN

Keep out of the reach of children. If swallowed, get medical help or contact a Poison Control Center right away.

DIRECTIONS:

- Apply liberally 15 minutes before sun exposure.
- Reapply:
  - After 80 minutes of swimming or sweating
  - Immediately after towel drying
  - At least every 2 hours
- Children under 6 months: Ask a doctor

Sun Protection Measures:

Spending time in the sun increases your risk of skin cancer and early skin aging. To decrease this risk, regularly use a sunscreen with a Broad Spectrum SPF value of 15 or higher and other sun protection measures including:

- Limit time in the sun, especially from 10 am-2 pm
- Wear long-sleeved shirts, pants, hats, and sunglasses

INACTIVE INGREDIENTS:

Alumina, Cyclohexasiloxane, Cyclopentasiloxane, Dimethicone, Dimethicone Crosspolymer, Dimethicone/Vinyl Dimethicone Crosspolymer, Dimethiconol, Iron Oxide (CI77491), Lauryl PEG/PPG-18/18-Methicone, Hydrogen Dimethicone, PEG-10 Dimethicone, Tetrahexyldecyl Ascorbate, Tocopheryl Acetate

OTHER INFORMATION:

- Protect this product from excessive heat and direct sun
- May stain some fabrics
- Cleanse thoroughly at nighttime
- PA+++

MANUFACTURED FOR:
Kathleeen Hutton MD
Newport Beach, CA 92660

WWW.HUTTONKLEIN.COM
800-909-0060

Principal Display Panel – 53 g Bottle Label

HUTTON KLEIN

HK
DERMATOLOGISTS

SPF 40

Mineral Based
Facial Sunscreen

- Free of Chemical Sunscreens
- Water-Resistant (80 Minutes)
- Broad Spectrum
- Unscented
- Oil and PABA Free

Tinted

Net. Wt. 1.8 oz./ 53 g